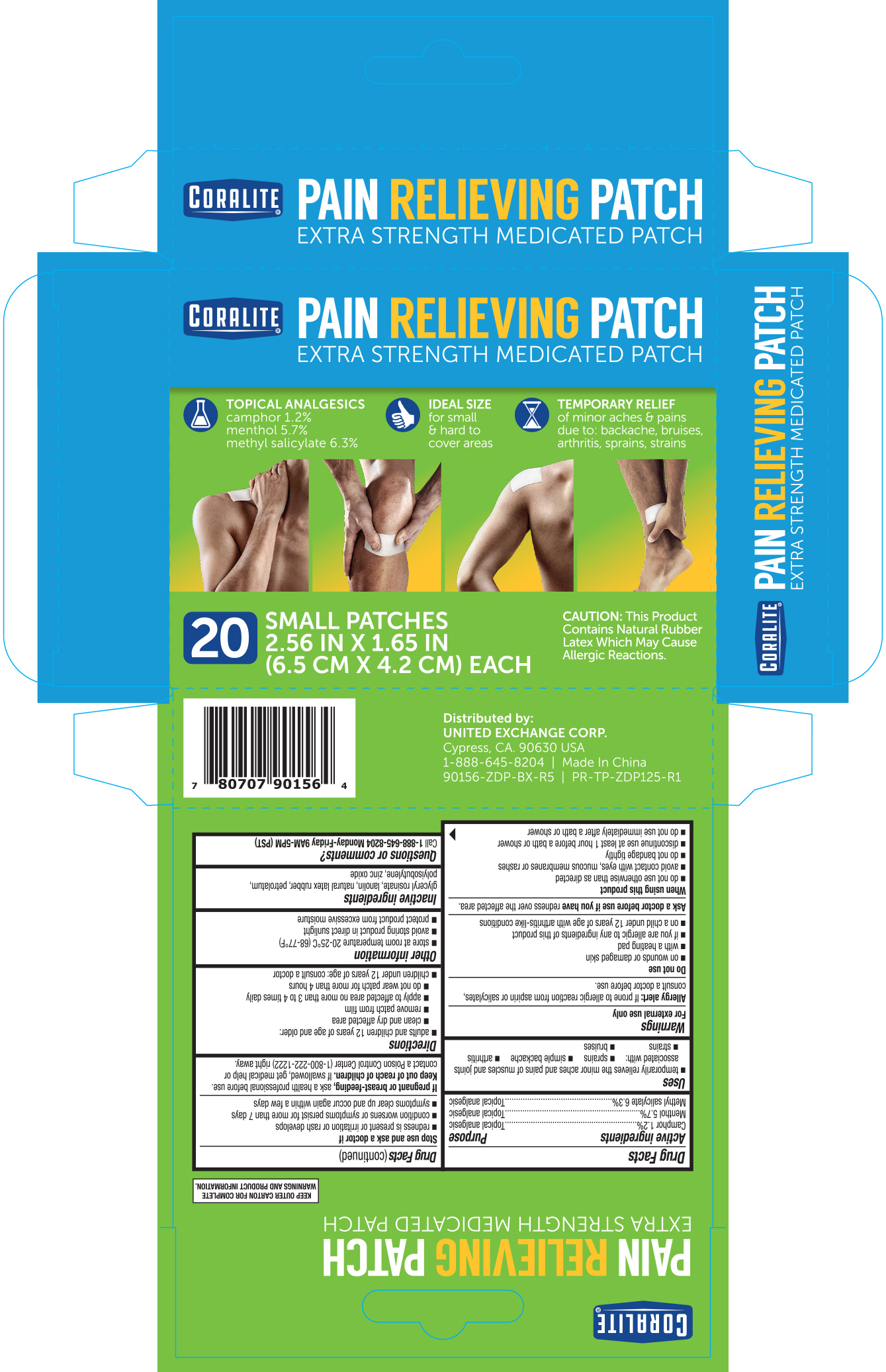 DRUG LABEL: Coralite Pain Relief
NDC: 65923-564 | Form: PATCH
Manufacturer: United Exchange Corp.
Category: otc | Type: HUMAN OTC DRUG LABEL
Date: 20251021

ACTIVE INGREDIENTS: CAMPHOR (SYNTHETIC) 1.2 g/100 g; MENTHOL 5.7 g/100 g; METHYL SALICYLATE 6.3 g/100 g
INACTIVE INGREDIENTS: ALUMINUM SILICATE; BUTYLATED HYDROXYTOLUENE; GLYCERYL ROSINATE; LANOLIN; NATURAL LATEX RUBBER; PARAFFIN; STYRENE/ISOPRENE/STYRENE BLOCK COPOLYMER; POLYISOBUTYLENE (85000 MW); TITANIUM DIOXIDE; POLYISOBUTYLENE (800000 MW); ZINC OXIDE

Coralite Small Pain Relief Patch 20 ct. 90156

Active ingredients Purpose

Camphor 1.2%........................................Topical Analgesic

Menthol 5.7%..........................................Topical Analgesic

Methyl Salicylate 6.3%............................Topical Analgesic

Uses

For temporary relief of minor aches & pains of muscles & joints associated with:

- arthritis
- simple backache
- strains
- bruises
- sprains

Warnings

For external use only

Allergy alert: If prone to allergic reaction from aspirin or salicylates, consult a doctor before use.

Do not use

- on wounds or damaged skin
- with a heating pad
- if you are allergic to any ingredients of this product
- on a child under 12 years of age with arthritis-like conditions

Ask a doctor before use if you have redness over the affected area.

When using this product

- do not use other than directed
- avoid contact with the eyes, mucous membranes or rashes
- do not bandage tightly
- discontinue use at least 1 hour before a bath or shower
- do not use immediately after a bath or shower

Stop use and ask a doctor if

- redness is present or irritation or rash develops
- condition worsens or symptoms persist for more than 7 days
- symptoms clear up and occur again within a few days

PREGNANCY OR BREAST FEEDING

If pregnant or breast-feeding, ask a health professional before use.

Keep out of reach of children. If swallowed, get medical help or conduct a Poision Control Center right away

Directions

adults and children 12 years of age and over:

- clean and dry affected area
- remove patch from film
- apply to affected area not more than 3 to 4 times daily
- do not wear patch for more than 4 hours
- children under 12 years of age: consult a doctor

Other information

- avoid storing product in direct sunlight
- protect from excessive moisture

Inactive ingredients

aluminum silicate, butylated hydroxytoluene, glyceryl rosinate, lanolin, natural rubber, paraffin, polyisobutylene (800000 mw), polyisobutylene (85000 mw), styrene-isoprene-styrene block copolymer, titanium dioxide, zinc oxide

DOSAGE AND ADMINISTRATION

Distributed by:

United Exchange Corp.

Cypress, CA 90630 USA

Made in China